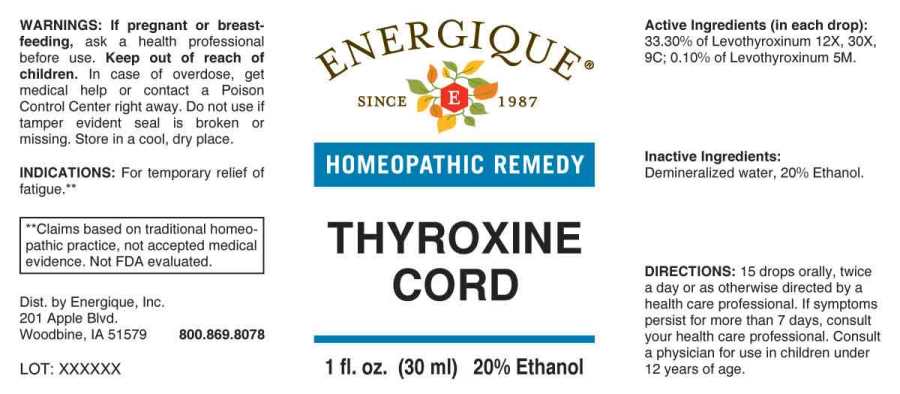 DRUG LABEL: Thyroxine Cord
NDC: 44911-0373 | Form: LIQUID
Manufacturer: Energique, Inc.
Category: homeopathic | Type: HUMAN OTC DRUG LABEL
Date: 20230126

ACTIVE INGREDIENTS: LEVOTHYROXINE 12 [hp_X]/1 mL
INACTIVE INGREDIENTS: WATER; ALCOHOL

Drug Facts:

ACTIVE INGREDIENT:

Levothyroxinum 12X, 30X, 9C, 5M.

INDICATIONS:

For temporary relief of fatigue.**

**Claims based on traditional homeopathic practice, not accepted medical evidence. Not FDA evaluated.

WARNINGS:

If pregnant or breastfeeding, ask a health professional before use.

Keep out of reach of children. In case of overdose, get medical help or contact a Poison Control Center right away.

Do not use if tamper evident seal is broken or missing.

Store in a cool, dry place.

Keep out of reach of children. In case of overdose, get medical help or contact a Poison Control Center right away.

DIRECTIONS:

15 drops orally, twice a day or as otherwise directed by a health care professional. If symptoms persist for more than 7 days, consult your health care professional. Consult a physician for use in children under 12 years of age.

INDICATIONS:

For temporary relief of fatigue.**

**Claims based on traditional homeopathic practice, not accepted medical evidence. Not FDA evaluated.

INACTIVE INGREDIENTS:

Demineralized water, 20% Ethanol.

QUESTIONS

Dist. by Energique, Inc.
201 Apple Blvd.
Woodbine, IA 51579 800.869.8078

PACKAGE LABEL DISPLAY:

ENERGIQUE

SINCE 1987

HOMEOPATHIC REMEDY

THYROXINE

CORD

1 fl. oz. (30 ml)